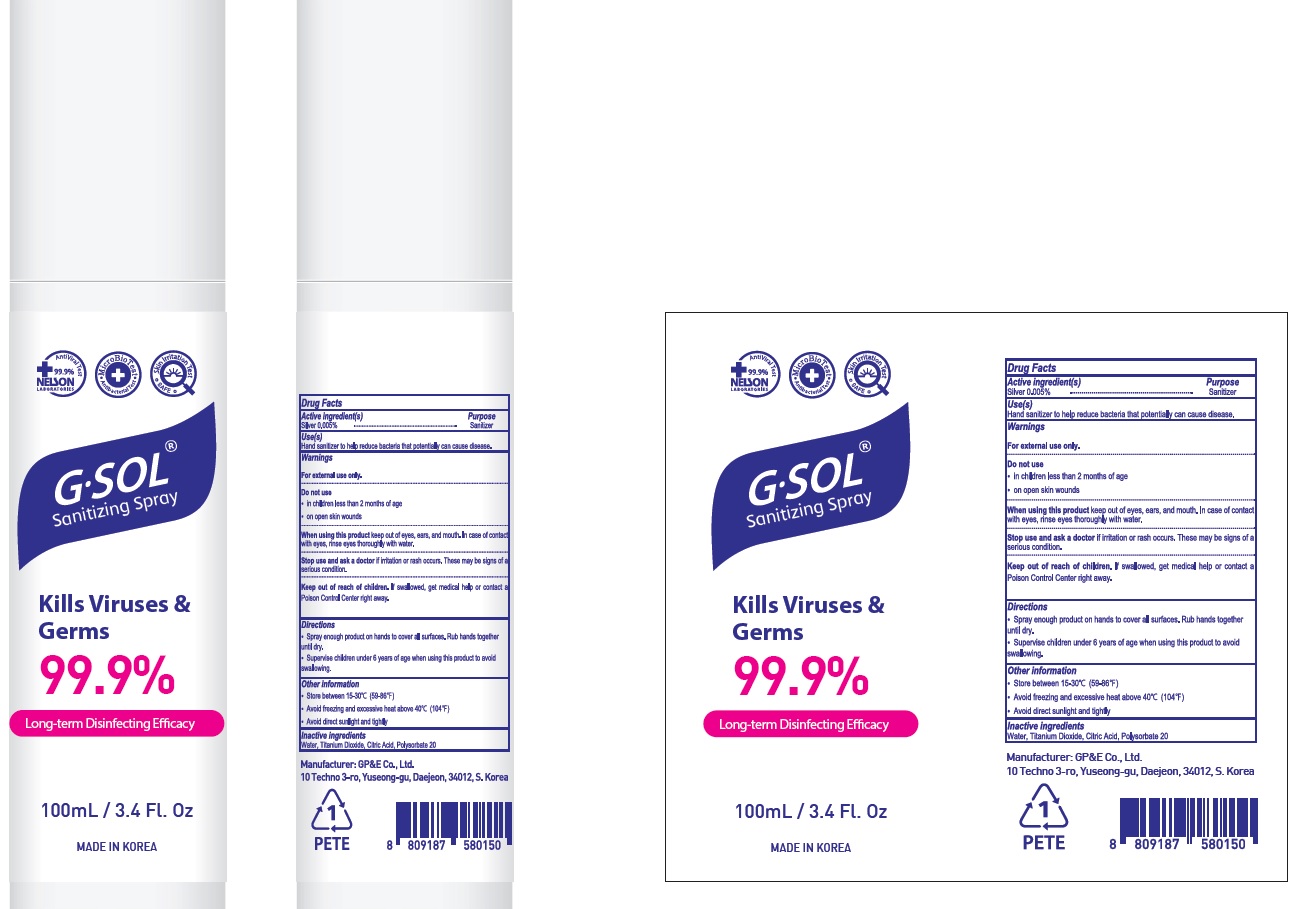 DRUG LABEL: G SOL Sanitizing
NDC: 81042-010 | Form: SPRAY
Manufacturer: GP&E Co., Ltd.
Category: otc | Type: HUMAN OTC DRUG LABEL
Date: 20220926

ACTIVE INGREDIENTS: Silver 0.005 g/100 mL
INACTIVE INGREDIENTS: Water; Titanium Dioxide; CITRIC ACID MONOHYDRATE; Polysorbate 20

ACTIVE INGREDIENT

Silver 0.005%

INACTIVE INGREDIENTS

Water, Titanium Dioxide, Citric Acid, Polysorbate 20

PURPOSE

Sanitizer

WARNINGS

For external use only.
--------------------------------------------------------------------------------------------------------
Do not use
• in children less than 2 months of age
• on open skin wounds
--------------------------------------------------------------------------------------------------------
When using this product keep out of eyes, ears, and mouth. In case of contact with eyes, rinse eyes thoroughly with water.
--------------------------------------------------------------------------------------------------------
Stop use and ask a doctor if irritation or rash occurs. These may be signs of a serious condition.
--------------------------------------------------------------------------------------------------------
Keep out of reach of children. If swallowed, get medical help or contact a Poison Control Center right away.

KEEP OUT OF REACH OF CHILDREN

If swallowed, get medical help or contact a Poison Control Center right away.

Use(s)

Hand sanitizer to help reduce bacteria that potentially can cause disease.

Directions

• Spray enough product on hands to cover all surfaces. Rub hands together until dry.
• Supervise children under 6 years of age when using this product to avoid swallowing.

Other information

• Store between 15-30C (59-86F)
• Avoid freezing and excessive heat above 40C (104F)
• Avoid direct sunlight and tightly